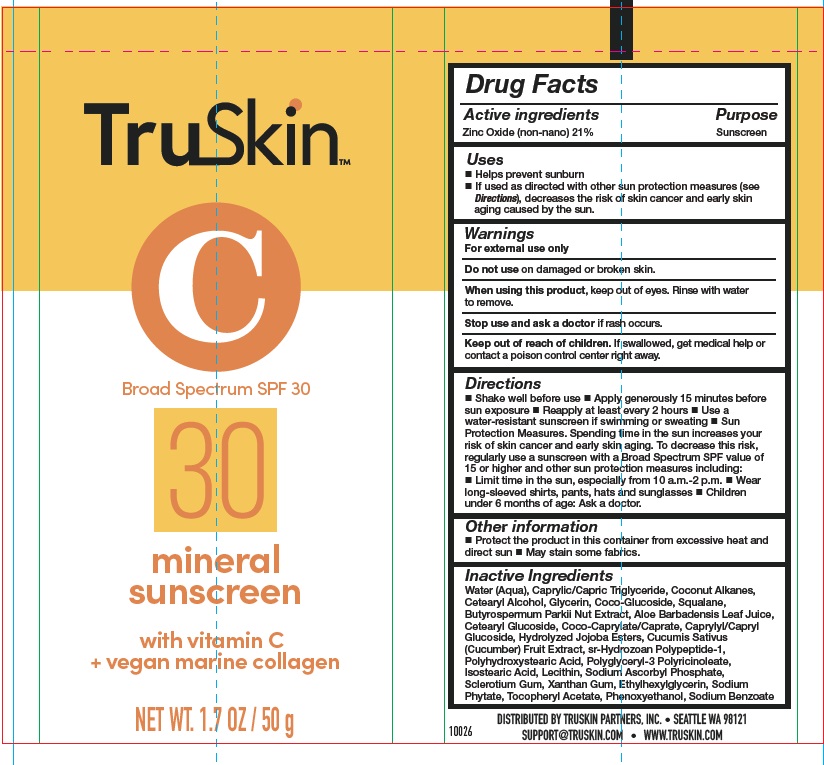 DRUG LABEL: Broad Spectrum SPF30 Mineral Sunscreen
NDC: 62742-4209 | Form: CREAM
Manufacturer: Allure Labs
Category: otc | Type: HUMAN OTC DRUG LABEL
Date: 20241209

ACTIVE INGREDIENTS: ZINC OXIDE 21 g/100 g
INACTIVE INGREDIENTS: COCO GLUCOSIDE; SHEANUT; ALOE VERA LEAF; COCO-CAPRYLATE/CAPRATE; CAPRYLYL/CAPRYL OLIGOGLUCOSIDE; SODIUM ASCORBYL PHOSPHATE; BETASIZOFIRAN; XANTHAN GUM; HYDROLYZED JOJOBA ESTERS (ACID FORM); CUCUMBER; POLYHYDROXYSTEARIC ACID (2300 MW); LECITHIN, SOYBEAN; ISOSTEARIC ACID; CETOSTEARYL ALCOHOL; GLYCERIN; PHYTATE SODIUM; .ALPHA.-TOCOPHEROL ACETATE; PHENOXYETHANOL; SODIUM BENZOATE; ETHYLHEXYLGLYCERIN; CETEARYL GLUCOSIDE; COCONUT ALKANES; POLYGLYCERYL-3 PENTARICINOLEATE; SQUALANE; WATER; MEDIUM-CHAIN TRIGLYCERIDES

Drug Facts

Active Ingredients

Zinc Oxide (non-nano) 21 %

Purpose

Sunscreen

Uses

Helps prevent sunburn

If used as directed with other Sun protection measures (see Directions), decreases the risk of skin cancer and early skin aging caused by the sun.

Warnings

For external use only

Do not use on damaged or broken skin.

When using this product keep out of eye Rinse with water to remove

Stop use and ask a doctor if rash occurs

Keep out of reach of children If swadlowed get medical help or contact a poison control center right away

Directions

Shake well before use

Apply generously 15 minutes before sun exposure

Reapply at least every 2 hours

Use a water-resistant sunscreen if swimming or sweating

Sun Protection Measures. Spending lime in the sun increases your risk of skin cancer and early skin aging. To decrease this risk, regularly use a sunscreen with abroad Spectrum SPF value of 15 or higher and other sun protet-Wn measures including

Limit time in the sun, especial& from 10 arn.-2 p.m

Wear long-sleeved shirts, pants, hats and sunglasses

Children under 6 months of age Ask a doctor.

Other information

'

Protect the product in this conitainer from excessive heat and direct sun

May stain some fabrics

Inactive Ingredients

Water (Aqua)

Caprylic/Capric Triglyceride

Coconut Alkanes

Cetearyl Alcohol

Glycerin

Coco-Glucoside

Squalane

Butyrospermum Parkii Nut Extract

Aloe Barbadensis Leaf Juice

Cetearyl Glucoside

Coco-Caprylate/Caprate

Caprylyl/Capryl Glucoside

Hydrolyzed Jojoba Esters

Cucumis Sativus (Cucumber) Fruit Extract

sr-Hydrozoan Polypeptide-1

Polyhydroxystearic Acid

Polyglyceryl-3 Polyricinoleate

Isostearic Acid

Lecithin

SodiuM Ascorbyl Phosphate

Sclerotium Gum

Xanthan Gum

Ethylhexylglycerin

Sodium Phytate

Tocopheryl Acetate

Phenoxyethanol

Sodium Benzoate